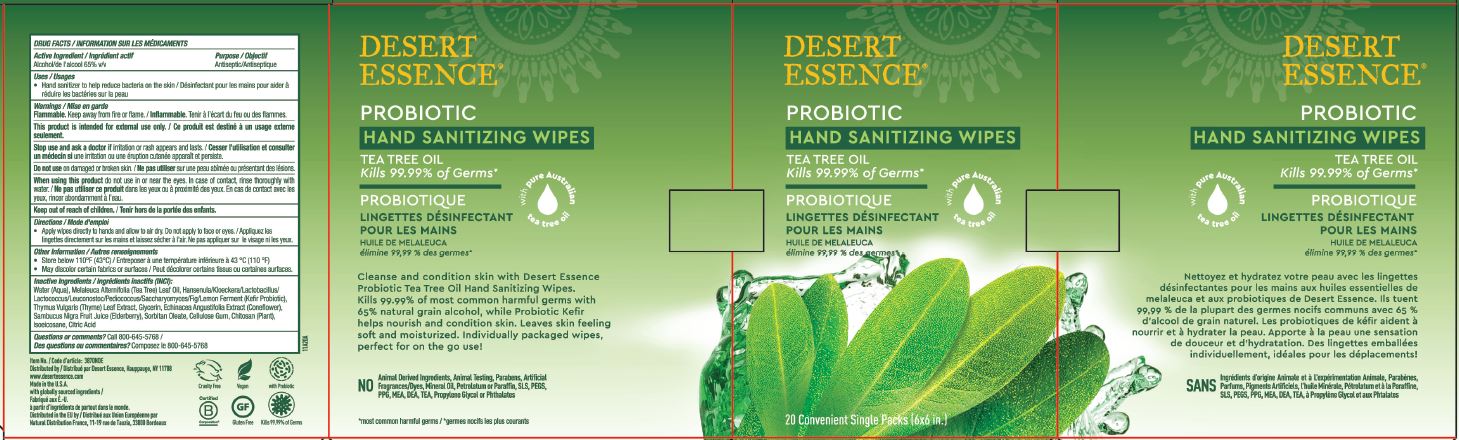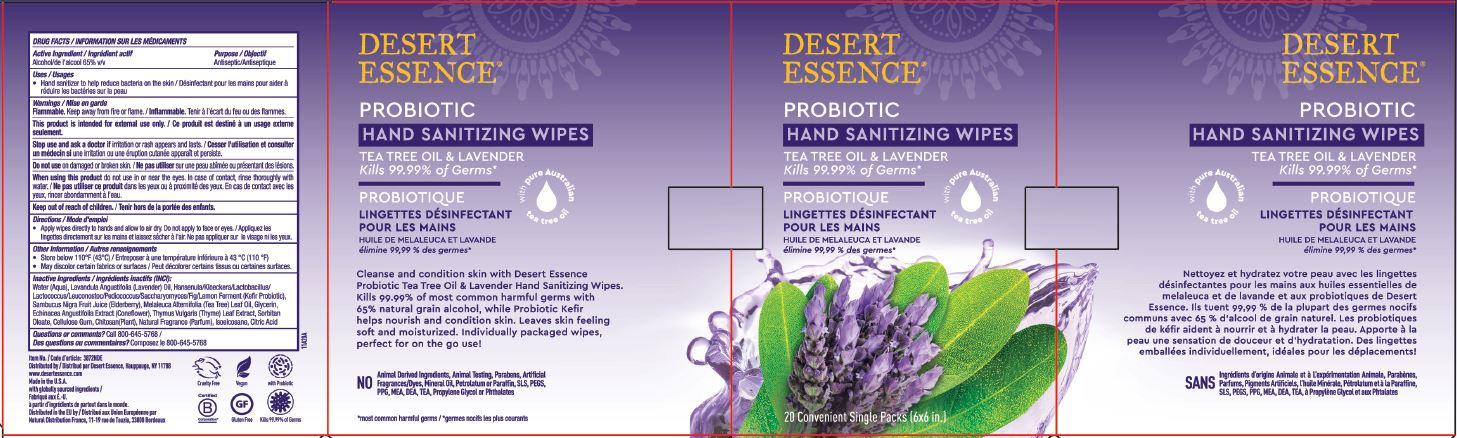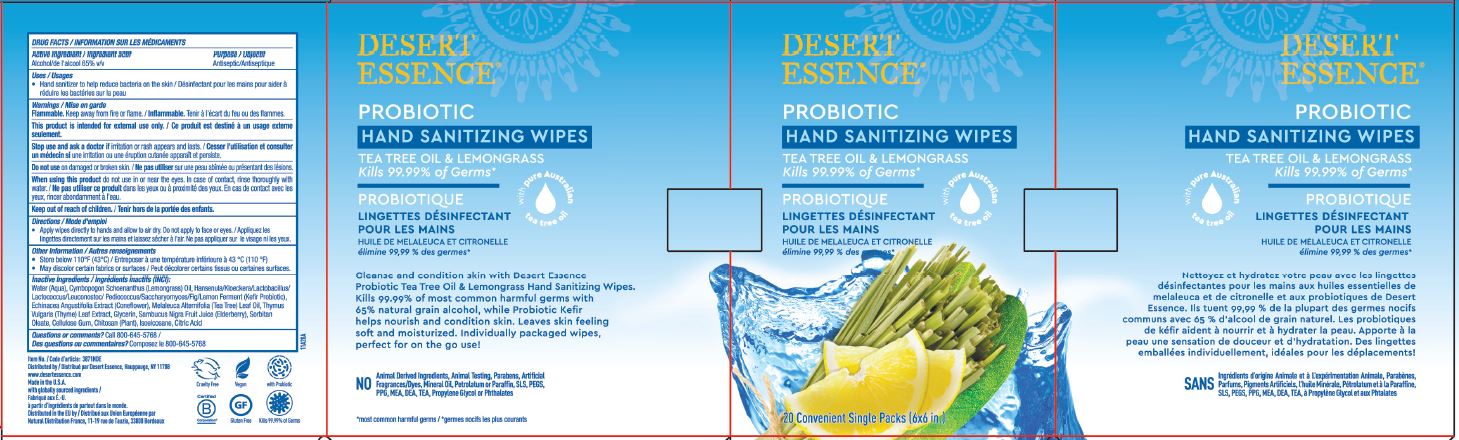 DRUG LABEL: PROBIOTIC HAND SANITIZING WIPES
NDC: 81001-102 | Form: SOLUTION
Manufacturer: Country Life Vitamins
Category: otc | Type: HUMAN OTC DRUG LABEL
Date: 20210102

ACTIVE INGREDIENTS: ALCOHOL 6.5 mL/1 1
INACTIVE INGREDIENTS: WATER; GLYCERIN; TEA TREE OIL; KEFIRAN; THYME; ECHINACEA ANGUSTIFOLIA; EUROPEAN ELDERBERRY JUICE; SORBITAN MONOOLEATE; CARBOXYMETHYLCELLULOSE SODIUM, UNSPECIFIED; CHITOSAN LOW MOLECULAR WEIGHT (20-200 MPA.S); ISOEICOSANE; ANHYDROUS CITRIC ACID; CYMBOPOGON SCHOENANTHUS OIL; LAVENDER OIL

DESERT ESSENCE PROBIOTIC HAND SANITIZER WIPES (Variants: Tea Tree Oil, Tea Tree & Lavender, Tea Tree & Lemongrass)

ACTIVE INGREDIENT

ALCOHOL 65% (V/V)

PURPOSE

ANTISEPTIC

USES

- HAND SANITIZER TO HELP REDUCE BACTERIA ON THE SKIN.

WARNINGS

FLAMMABLE. KEEP AWAY FROM FIRE OR FLAME.

THIS PRODUCT IS INTENDED FOR EXTERNAL USE ONLY.

STOP USE AND ASK A DOCTOR IF IRRITATION OR RASH APPEARS AND LASTS.

DO NOT USE ON DAMAGED OR BROKEN SKIN.

WHEN USING THIS PRODUCT DO NOT USE IN OR NEAR THE EYES. IN CASE OF CONTACT, RINSE THOROUGHLY WITH WATER.

KEEP OUT OF REACH OF CHILDREN. IF SWALLOWED, GET MEDICAL HELP OR CONTACT A POISON CONTROL CENTER RIGHT AWAY.

DIRECTIONS

- APPLY WIPES DIRECTLY TO HANDS AND ALLOW TO AIR DRY. DO NOT APPLY TO FACE OR EYES.

OTHER INFORMATION

- STORE BELOW 110°F (43°C)
- MAY DISCOLOR CERTAIN FABRICS OR SURFACES

INACTIVE INGREDIENTS

TEA TREE & LEMONGRASS: WATER (AQUA), CYMBOPOGON SCHOENANTHUS (LEMONGRASS) OIL, HANSENULA/KLOECKERA/LACTOBACILLUS/LACTOCOCCUS/LEUCONOSTOC/PEDIOCOCCUS/SACCHARYOMYCES/FIG/LEMON FERMENT (KEFIR PROBIOTIC), ECHINACEA ANGUSTIFOLIA EXTRACT (CONEFLOWER), MELALEUCA ALTERNIFOLIA (TEA TREE) LEAF OIL, THYMUS VULGARIS (THYME) LEAF EXTRACT, GLYCERIN, SAMBUCUS NIGRA FRUIT JUICE (ELDERBERRY), SORBITAN OLEATE, CELLULOSE GUM, CHITOSAN (PLANT), ISOEICOSANE, CITRIC ACID

TEA TREE OIL: WATER (AQUA), MELALEUCA ALTERNIFOLIA (TEA TREE) LEAF OIL, HANSENULA/KLOECKERA/LACTOBACILLUS/LACTOCOCCUS/LEUCONOSTOC/PEDIOCOCCUS/SACCHARYOMYCES/FIG/LEMON FERMENT (KEFIR PROBIOTIC), THYMUS VULGARIS (THYME) LEAF EXTRACT, GLYCERIN, ECHINACEA ANGUSTIFOLIA EXTRACT (CONEFLOWER), SAMBUCUS NIGRA FRUIT JUICE (ELDERBERRY), SORBITAN OLEATE, CELLULOSE GUM, CHITOSAN (PLANT), ISOEICOSANE, CITRIC ACID

TEA TREE & LAVENDER: WATER (AQUA), LAVANDULA ANGUSTIFOLIA (LAVENDER) OIL, HANSENULA/KLOECKERA/LACTOBACILLUS/LACTOCOCCUS/LEUCONOSTOC/PEDIOCOCCUS/SACCHARYOMYCES/FIG/LEMON FERMENT (KEFIR PROBIOTIC), SAMBUCUS NIGRA FRUIT JUICE (ELDERBERRY), MELALEUCA ALTERNIFOLIA (TEA TREE) LEAF OIL, GLYCERIN, ECHINACEA ANGUSTIFOLIA EXTRACT (CONEFLOWER), THYMUS VULGARIS (THYME) LEAF EXTRACT, SORBITAN OLEATE, CELLULOSE GUM, CHITOSAN (PLANT), NATURAL FRAGRANCE (PARFUM), ISOEICOSANE, CITRIC ACID

QUESTIONS?

CALL 800-645-5768